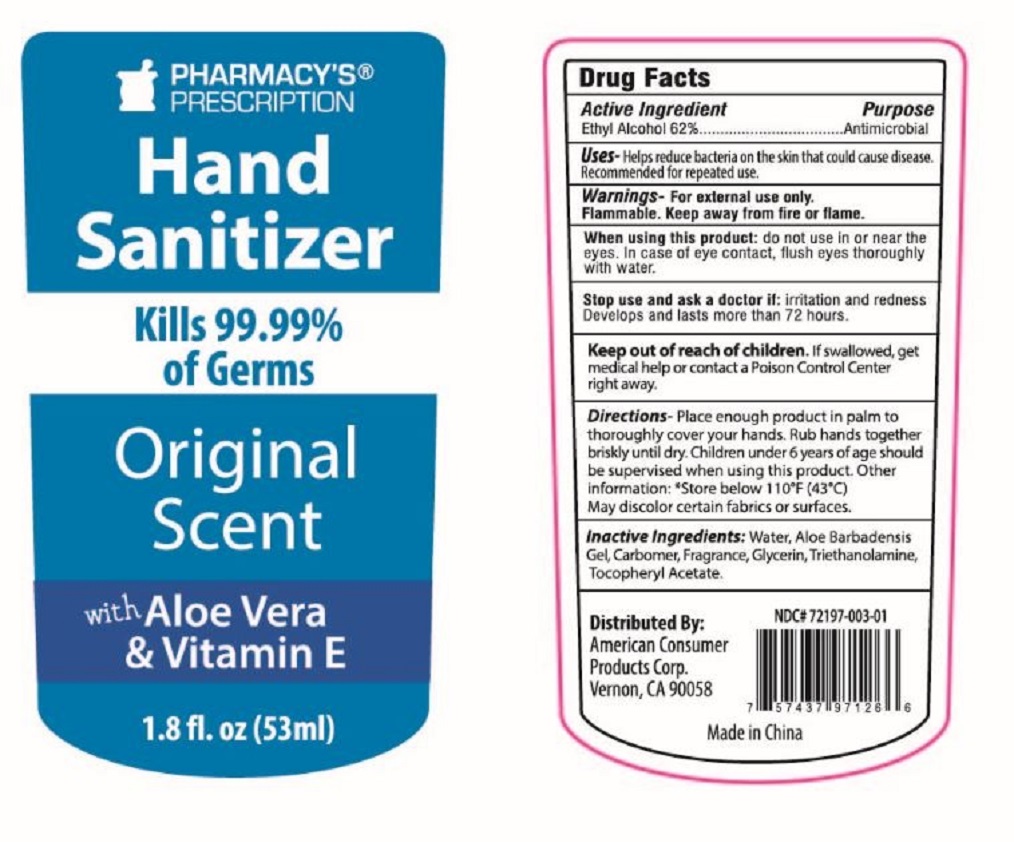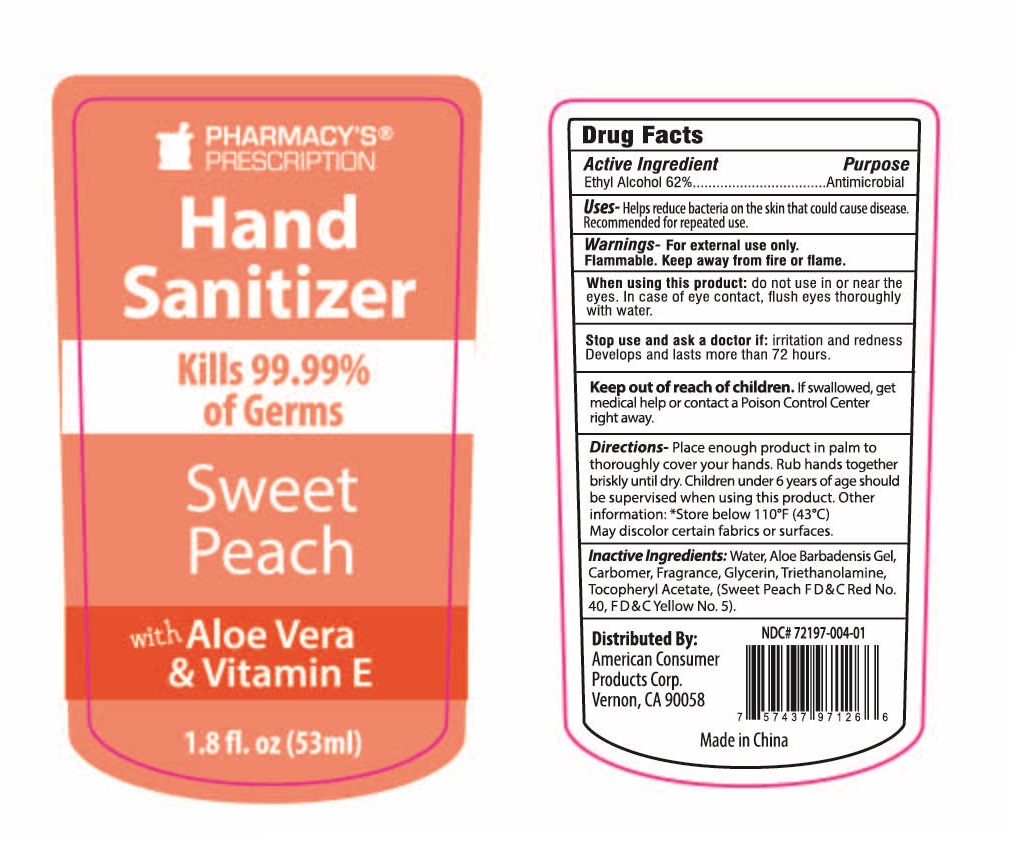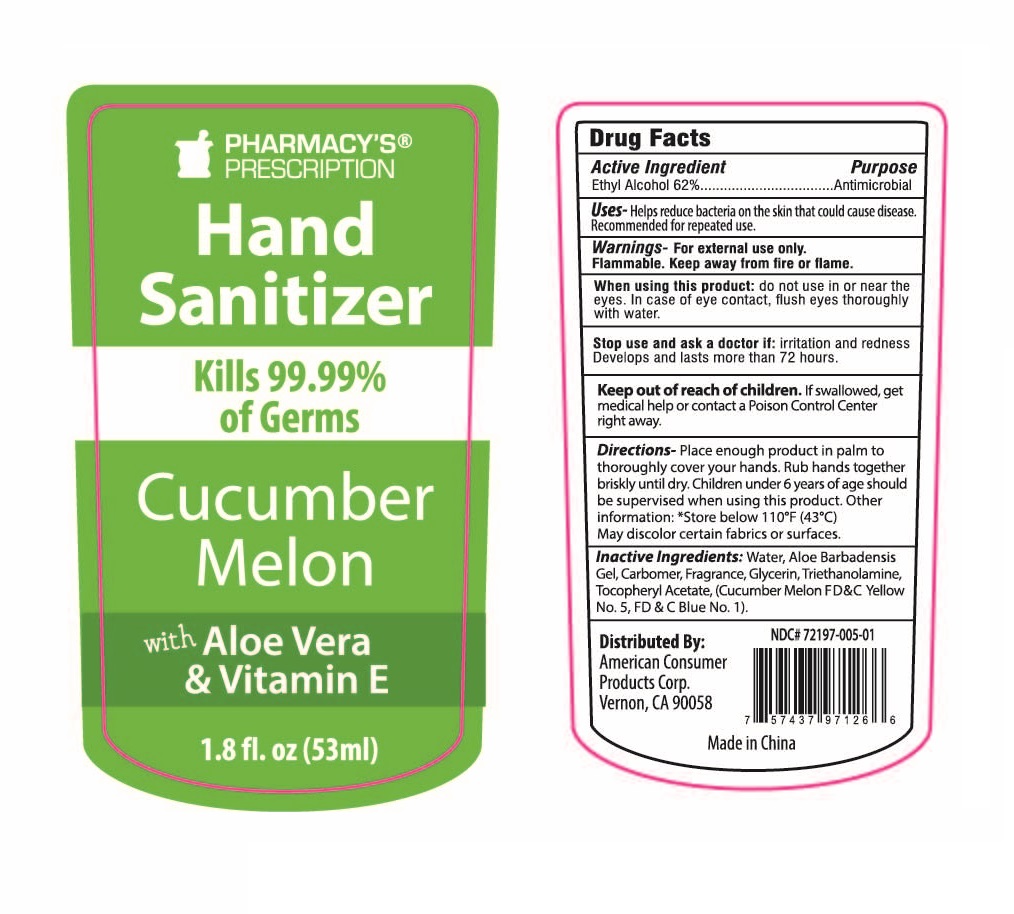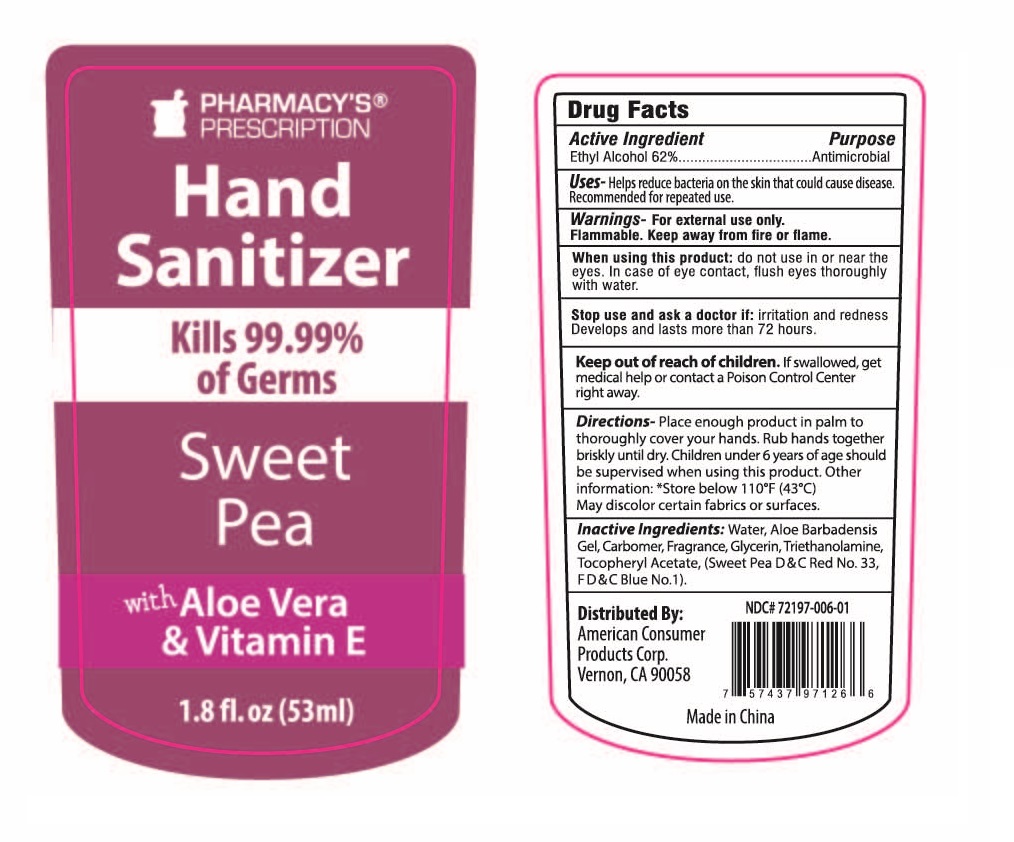 DRUG LABEL: PHARMACYS PRESCRIPTION 1.8OZ HAND SANITIZER CUCUMBER MELON
NDC: 72197-005 | Form: GEL
Manufacturer: American Consumer Products Corp
Category: otc | Type: HUMAN OTC DRUG LABEL
Date: 20191231

ACTIVE INGREDIENTS: ALCOHOL 62 mL/100 mL
INACTIVE INGREDIENTS: .ALPHA.-TOCOPHEROL ACETATE, D-; GLYCERIN; TROLAMINE; CARBOMER 980; ALOE ARBORESCENS WHOLE; WATER

Pharmacy's Prescription 1.8OZ Hand Sanitizer(s)

Active Ingredient

Active Ingredient: Ethyl Alcohol 62%

Purpose

Purpose: Antimicrobial

Warnings

Warnings - For external use only. Flammable. Keep away from fire or flame.

Stop Use

Stop use and ask a doctor if: irritation and redness Develops and lasts more than 72 hours.

Keep out of reach of children. If swallowed, get medical help or contact a Poison Control Center right away.

Directions

Directions - Place enough product in palm to thoroughly cover your hands. Rub hands together briskly undtil dry. Children under 6 years of age should be supervised when using this product. Other information: *Store below 110o F (43o C) May discolor certain fabrics or surfaces.

Inactive Ingredients

Inactive Ingredients: Water, Aloe Barbadensis Gel, Carbomer, Fragrance, Glycerin, Triethanolamine, Tocopheryl Acetate.

Indications & Usage Section

When using this product: do not use in or near the eyes. In case of eye contact, flush eyes thoroughly with water.